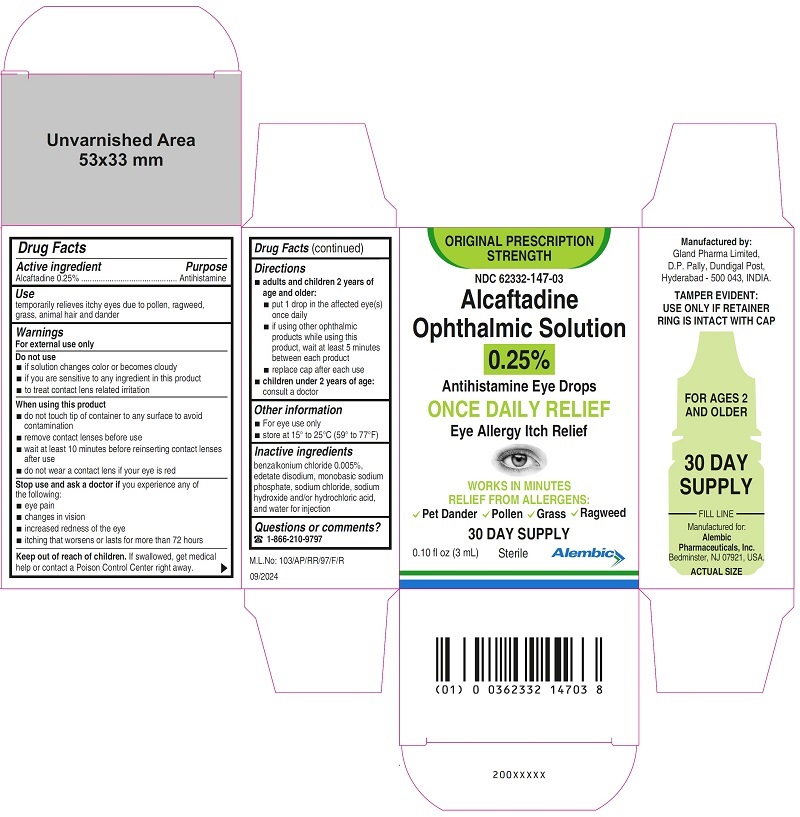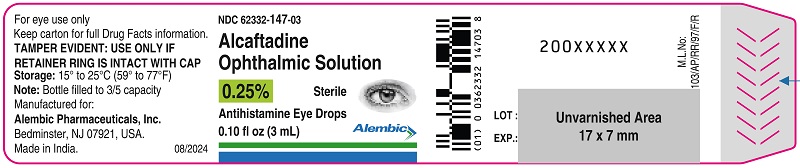 DRUG LABEL: alcaftadine
NDC: 62332-147 | Form: SOLUTION/ DROPS
Manufacturer: Alembic Pharmaceuticals Inc.
Category: otc | Type: Human OTC Drug Label
Date: 20241007

ACTIVE INGREDIENTS: ALCAFTADINE 2.5 mg/1 mL
INACTIVE INGREDIENTS: BENZALKONIUM CHLORIDE; EDETATE DISODIUM; SODIUM PHOSPHATE, MONOBASIC; WATER; SODIUM CHLORIDE; SODIUM HYDROXIDE; HYDROCHLORIC ACID

.

ACTIVE INGREDIENT

Alcaftadine 0.25%

PURPOSE

Antihistamine

USE

temporarily relieves itchy eyes due to pollen, ragweed, grass, animal hair and dander

WARNINGS

For external use only

DO NOT USE

- if solution changes color or becomes cloudy
- if you are sensitive to any ingredient in this product
- to treat contact lens related irritation

WHEN USING THIS PRODUCT

- do not touch tip of container to any surface to avoid contamination
- remove contact lenses before use
- wait at least 10 minutes before reinserting contact lenses after use
- do not wear a contact lens if your eye is red

STOP USE AND ASK DOCTOR IF

you experience any of the following:

- eye pain
- changes in vision
- increased redness of the eye
- itching worsens or lasts for more than 72 hours

KEEP OUT OF REACH OF CHILDREN

If swallowed, get medical help or contact a Poison Control Center right away.

DIRECTIONS

- adults and children 2 years of age and older:
  - put 1 drop in the affected eye(s) once daily
  - if using other ophthalmic products while using this product, wait at least 5 minutes between each product
  - replace cap after each use
- children under 2 years of age: consult a doctor

OTHER INFORMATION

- For eye use only
- store at 15° to 25°C (59° to 77°F)

INACTIVE INGREDIENTS

benzalkonium chloride 0.005%, edetate disodium, monobasic sodium phosphate, sodium chloride, sodium hydroxide and/or hydrochloric acid, and water for injection

QUESTIONS OR COMMENTS?

(1-866-210-9797

Manufactured by:
Gland Pharma Limited,
D.P. Pally, Dundigal Post,
Hyderabad - 500 043, INDIA.

Manufactured for:
Alembic Pharmaceuticals, Inc.
Bedminster, NJ 07921, USA.

Revision: 09/2024

PRINCIPAL DISPLAY PANEL

Container Label - 0.25% (3 mL)
NDC 62332-147-03
Alcaftadine Ophthalmic Solution, 0.25%
Antihistamine Eye Drops
Eye Allergy Itch Relief
Sterile
0.10 fl oz (3 mL)

Carton Label - 0.25% (3 mL)

NDC 62332-147-03
ORIGINAL PRESCRIPTION STRENGTH
Alcaftadine Ophthalmic Solution, 0.25%
Antihistamine Eye Drops
ONCE DAILY RELIEF
Eye Allergy Itch Relief
Sterile
30 DAY SUPPLY
0.10 fl oz (3 mL)